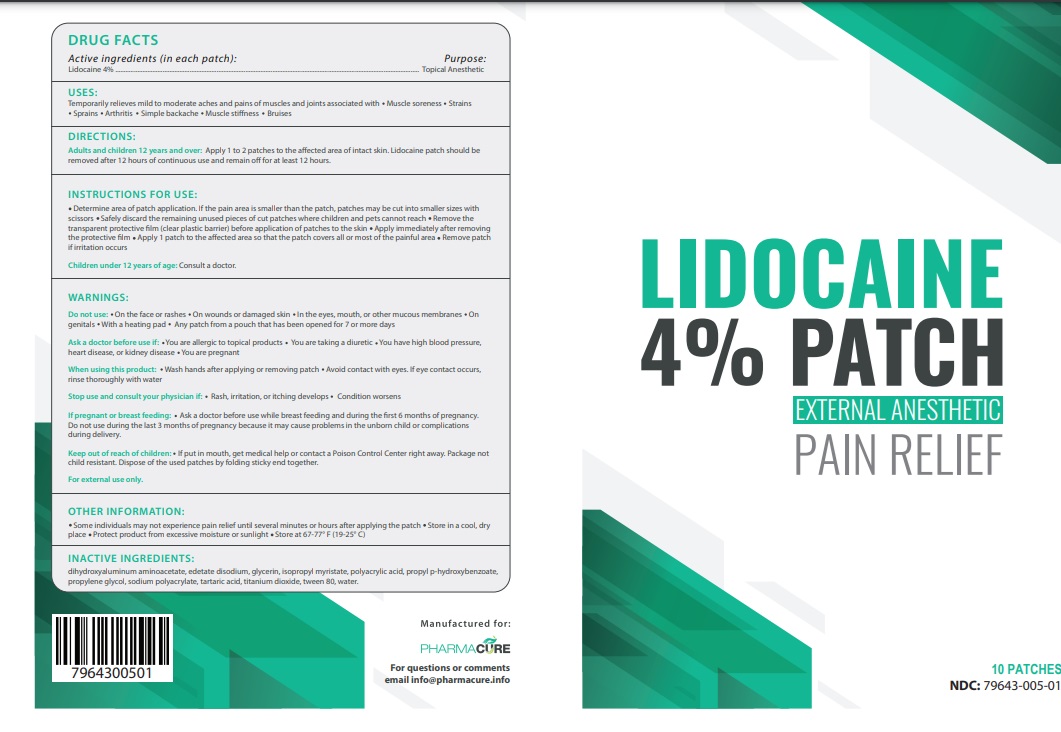 DRUG LABEL: LIDOCAINE
NDC: 79643-005 | Form: PATCH
Manufacturer: PHARMACURE LLC
Category: otc | Type: HUMAN OTC DRUG LABEL
Date: 20251006

ACTIVE INGREDIENTS: LIDOCAINE 4 g/100 g
INACTIVE INGREDIENTS: DIHYDROXYALUMINUM AMINOACETATE; EDETATE DISODIUM; GLYCERIN; ISOPROPYL MYRISTATE; POLYACRYLIC ACID (250000 MW); PROPYLPARABEN; PROPYLENE GLYCOL; SODIUM POLYACRYLATE (2500000 MW); TARTARIC ACID; TITANIUM DIOXIDE; POLYSORBATE 80; WATER

Active Ingredient

Lidocaine 4%

Purpose

Topical Anesthetic

Uses

Temporarily relieves mild to moderate aches and pains of muscles and joints associated with muscle soreness, strains, sprains, arthritis, simple backache, muscle stiffness, bruises

Warnings

Do not use on the face or rashes, on wounds or damaged skin, in the eyes, mouth, or other mucous membranes, on genitals, with a heating pad, any patch from a pouch that has been opened for 7 or more days.

Ask a doctor before use if you are allergic to topical products, you are taking a diuretic, you have high blood pressure, heart disease, kidney disease, or you are pregnant.

When using this product wash hands after applying or removing patch. Avoid contact with eyes. If eye contact occurs, rinse thoroughly with water.

Stop use and consult your physician if rash, irritation, or itching develops, or condition worsens.

If pregnant or breastfeeding, ask a doctor before use while breastfeeding and during the first 6 months of pregnancy. Do not use during the last 3 months of pregnancy because it may cause problems in the unborn child or complications during delivery.

For external use only

Keep out of reach of children.If product is put in mouth, get medical help of contact a Poison Control Center right away. Package is not child resistant. Dispose of the used patches by folding sticky ends together.

Directions

Adults and children 12 years and over: apply 1 to 2 patches to the affected area of intact skin. Lidocaine patch should be removed after 12 hours of continuous use and remain off for at least 12 hours.

INSTRUCTIONS FOR USE

- Determine area of patch application. If the pain area is smaller than the patch, patches may be cut into smaller sizes with scissors
- Safely discard the remaining unused pieces of cut patches where children and pets cannot reach
- Remove the transparent protective film (clear plastic barrier) before application of patches to the skin
- Apply immediately after removing the protective film Apply 1 patch to the affected area so that the patch covers all or most of the painful area
- Remove patch if irritation occurs

Children under 12 years of age: Consult a doctor.

Inactive ingredients

dihydroxyaluminum aminoacetate, edetate disodium, glycerin, isopropyl myristate, polyacrylic acid, propyl p-hydroxybenzoate, propylene glycol, sodium polyacrylate, tartaric acid, titanium dioxide, tween 80, water

Other information

Some individuals may not experience pain relief until several minutes or hours after applying the patch. Store in a cool, dry place. Protect the product from excessive moisture or sunlight. Store at 67-77°F (19-25°C).